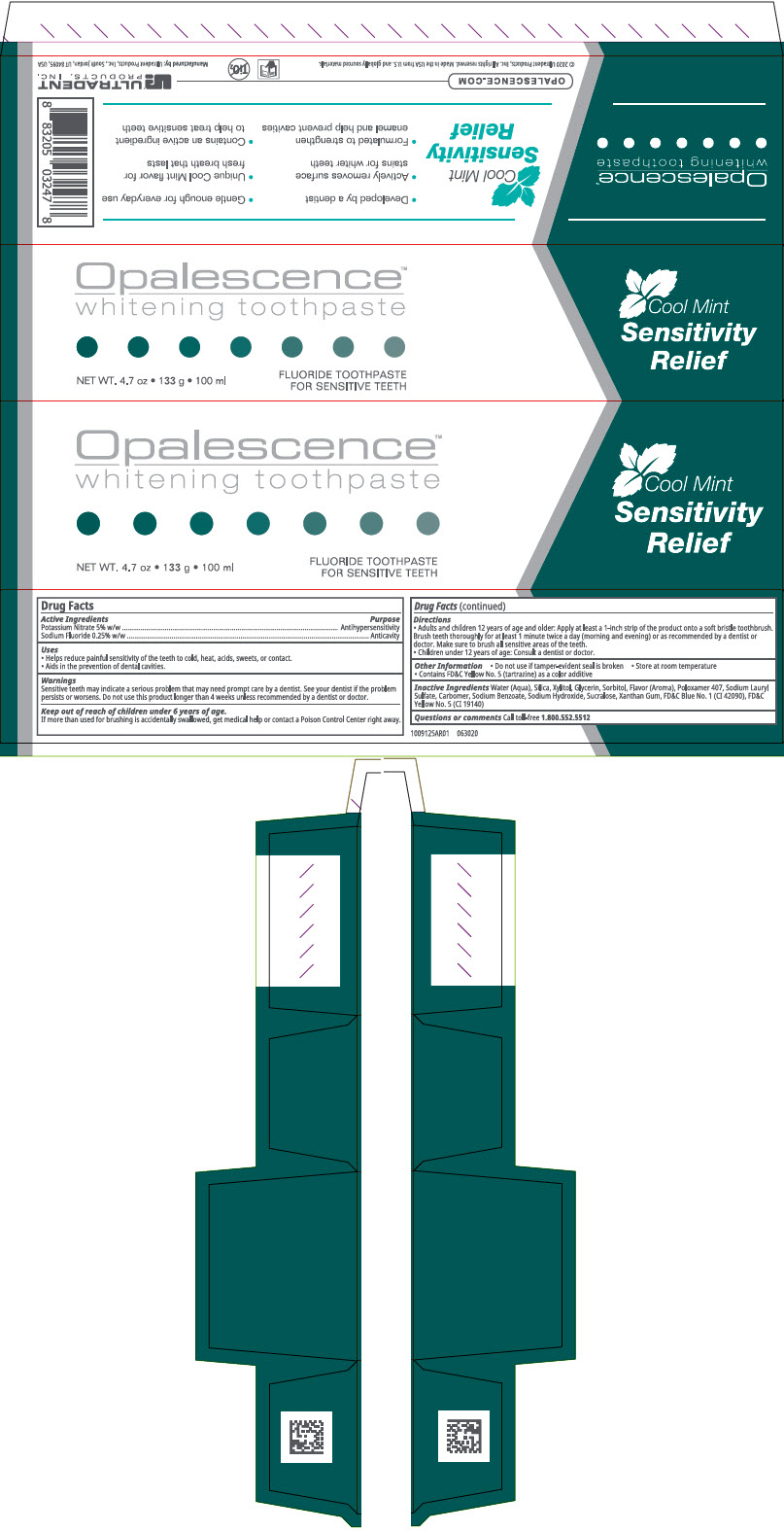 DRUG LABEL: Opalescence Sensitivity Relief Whitening
NDC: 51206-308 | Form: GEL, DENTIFRICE
Manufacturer: Ultradent Products, Inc.
Category: otc | Type: HUMAN OTC DRUG LABEL
Date: 20251117

ACTIVE INGREDIENTS: POTASSIUM NITRATE 50 mg/1 g; SODIUM FLUORIDE 1.1 mg/1 g
INACTIVE INGREDIENTS: GLYCERIN; XANTHAN GUM; WATER; SORBITOL; SODIUM HYDROXIDE; XYLITOL; SODIUM BENZOATE; SUCRALOSE; SILICON DIOXIDE; METHYL SALICYLATE; SODIUM LAURYL SULFATE

Opalescence™ Sensitivity Relief Whitening Toothpaste

Drug Facts

ACTIVE INGREDIENT

Active Ingredients | Purpose
Potassium Nitrate 5% w/w | Antihypersensitivity
Sodium Fluoride 0.25% w/w | Anticavity

Uses

- Helps reduce painful sensitivity of the teeth to cold, heat, acids, sweets, or contact.
- Aids in the prevention of dental cavities.

Warnings

Sensitive teeth may indicate a serious problem that may need prompt care by a dentist. See your dentist if the problem persists or worsens. Do not use this product longer than 4 weeks unless recommended by a dentist or doctor.

Keep out of reach of children under 6 years of age.

If more than used for brushing is accidentally swallowed, get medical help or contact a Poison Control Center right away.

Directions

- Adults and children 12 years of age and older: Apply at least a 1-inch strip of the product onto a soft bristle toothbrush. Brush teeth thoroughly for at least 1 minute twice a day (morning and evening) or as recommended by a dentist or doctor. Make sure to brush all sensitive areas of the teeth.
- Children under 12 years of age: Consult a dentist or doctor.

Other Information

- Do not use if tamper-evident seal is broken
- Store at room temperature
- Contains FD&C Yellow No. 5 (tartrazine) as a color additive

Inactive Ingredients

Water (Aqua), Silica, Xylitol, Glycerin, Sorbitol, Flavor (Aroma), Poloxamer 407, Sodium Lauryl Sulfate, Carbomer, Sodium Benzoate, Sodium Hydroxide, Sucralose, Xanthan Gum, FD&C Blue No. 1 (CI 42090), FD&C Yellow No. 5 (CI 19140)

Questions or comments

Call toll-free 1.800.552.5512

Manufactured by:Ultradent Products, Inc., South Jordan, UT 84095, USA

PRINCIPAL DISPLAY PANEL - 133 g Tube Carton

Opalescence™
whitening toothpaste

Cool Mint
Sensitivity
Relief

NET WT. 4.7 oz • 133 g • 100 ml

FLUORIDE TOOTHPASTE
FOR SENSITIVE TEETH